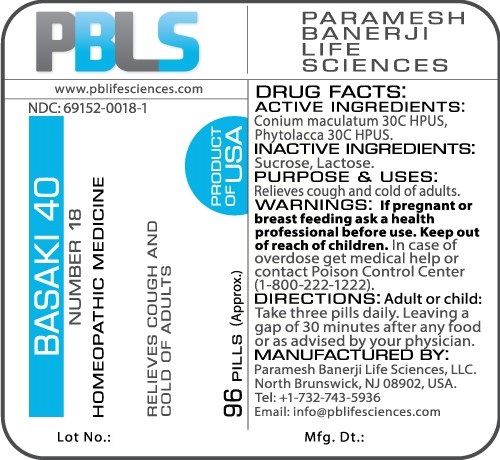 DRUG LABEL: Basaki 40 (Number 18)
NDC: 69152-0018 | Form: PELLET
Manufacturer: Paramesh Banerji Life Sciences LLC
Category: homeopathic | Type: HUMAN OTC DRUG LABEL
Date: 20161109

ACTIVE INGREDIENTS: CONIUM MACULATUM FLOWERING TOP 30 [hp_C]/1 1; PHYTOLACCA AMERICANA ROOT 30 [hp_C]/1 1
INACTIVE INGREDIENTS: SUCROSE; LACTOSE

DRUG FACTS: Active Ingredients

Conium maculatum 30C HPUS, Phytolacca 30C HPUS

Inactive Ingredients

Sucrose, Lactose

Purpose

Relieves cough and cold of adults

Uses

Relieves cough and cold of adults

Warnings

If pregnant or breast feeding ask a health professional before use.

Keep out of reach of children. In case of overdose, get medical help or contact a Poison Control Center (1-800-222-1222) right away.

Direction

Adult or child: Take three pills daily. Leaving a gap of 30 minutes after any food or as advised by your physician.

Manufactured by

Paramesh Banerji Life Sciences, LLC.

North Brunswick, NJ 08902, USA.

Tel: +1-732-743-5936

Email: info@pblifesciences.com

Principal Display Panel

NDC: 69152-0018-1

Basaki 40

Number 18

Homeopathic Medicine

Relieves cough and cold of adults

96 Pills (Approx.)

Product of USA